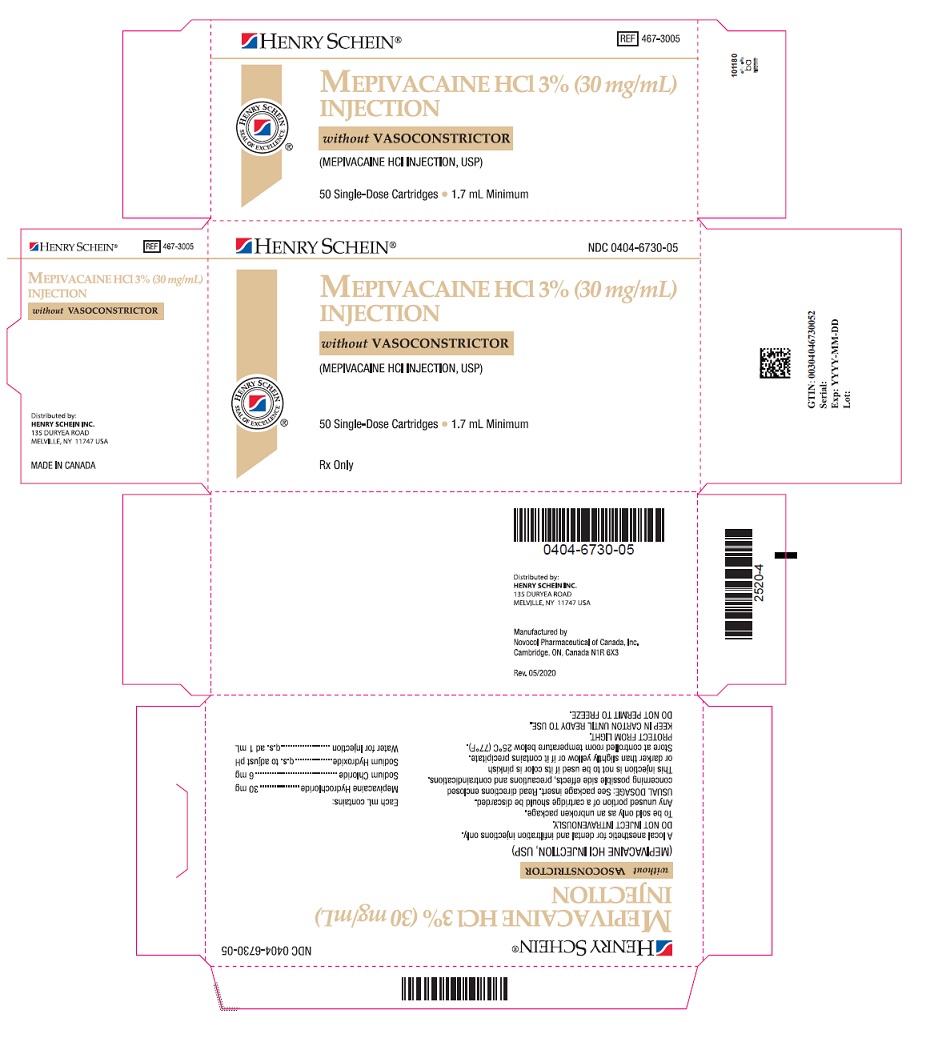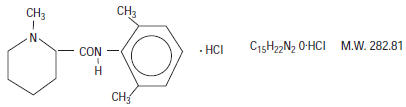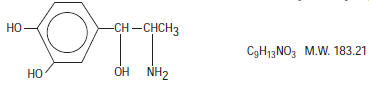 DRUG LABEL: Mepivacaine Hydrochloride
NDC: 0404-6730 | Form: INJECTION, SOLUTION
Manufacturer: Henry Schein Inc.
Category: prescription | Type: HUMAN PRESCRIPTION DRUG LABEL
Date: 20240221

ACTIVE INGREDIENTS: Mepivacaine Hydrochloride 30 mg/1 mL
INACTIVE INGREDIENTS: Sodium Chloride 6 mg/1 mL; Sodium Hydroxide; Water

Mepivacaine HCl 3% (30 mg/mL)
(Mepivacaine Hydrochloride Injection, USP)
Mepivacaine HCl 2% (30 mg/mL)
(with Levonordefrin 1:20,000)
(Mepivacaine Hydrochloride and Levonordefrin Injection, USP)

Rx Only

THESE SOLUTIONS ARE INTENDED FOR DENTAL USE ONLY.

DESCRIPTION

Mepivacaine Hydrochloride, a tertiary amine used as a local anesthetic, is 1-methyl-2', 6' - pipecoloxylidide monohydrochloride with the following structural formula:

It is a white, crystalline, odorless powder soluble in water, but very resistant to both acid and alkaline hydrolysis.

Levonordefrin, a sympathomimetic amine used as a vasoconstrictor in local anesthetic solution, is (-)-α-(1-Aminoethyl)-3, 4-dihydroxybenzyl alcohol with the following structural formula:

It is a white or buff-colored crystalline solid, freely soluble in aqueous solutions of mineral acids, but practically insoluble in water;

DENTAL CARTRIDGES MAY NOT BE AUTOCLAVED.

Mepivacaine hydrochloride injection 3% (30 mg/mL) and Mepivacaine hydrochloride 2% (20 mg/mL) with levonordefrin 1:20,000 injection are sterile solutions for injection.

COMPOSITION: | CARTRIDGE
Each mL contains: | 2% | 3%
Mepivacaine Hydrochloride | 20 mg | 30 mg
Levonordefrin | 0.05 mg | -
Sodium Chloride | 4 mg | 6 mg
Potassium metabisulfite | 1.2 mg | -
Edetate disodium | 0.25 mg | -
Sodium Hydroxide q.s. ad pH; Hydrochloric Acid | 0.5 mg | -
Water For Injection, qs. ad. | 1 mL | 1 mL
The pH of the 2% cartridge solution is adjusted between 3.3 and 5.5 with NaOH.
The pH of the 3% cartridge solution is adjusted between 4.5 and 6.8 with NaOH.

CLINICAL PHARMACOLOGY

Mepivacaine stabilizes the neuronal membrane and prevents the initiation and transmission of nerve impulses, thereby effecting local anesthesia.

Mepivacaine is rapidly metabolized, with only a small percentage of the anesthetic (5 to 10 percent) being excreted unchanged in the urine. Mepivacaine because of its amide structure, is not detoxified by the circulating plasma esterases. The liver is the principal site of metabolism, with over 50 percent of the administered dose being excreted into the bile as metabolites. Most of the metabolized Mepivacaine is probably resorbed in the intestine and then excreted into the urine since only a small percentage is found in the feces. The principal route of excretion is via the kidney. Most of the anesthetic and its metabolites are eliminated within 30 hours. It has been shown that hydroxylation and N-demethylation, which are detoxification reactions, play important roles in the metabolism of the anesthetic. Three metabolites of Mepivacaine have been identified from adult humans: two phenols, which are excreted almost exclusively as their glucuronide conjugates, and the N-demethylated compound (2', 6' - pipecoloxylidide).

The onset of action is rapid (30 to 120 seconds in the upper jaw; 1 to 4 minutes in the lower jaw) and Mepivacaine HCl 3% (30 mg/mL) will ordinarily provide operating anesthesia of 20 minutes in the upper jaw and 40 minutes in the lower jaw.

Mepivacaine HCl 2% (20 mg/mL) with Levonordefrin 1:20,000 provides anesthesia of longer duration for more prolonged procedures, 1 hour to 2.5 hours in the upper jaw and 2.5 hours to 5.5 hours in the lower jaw.

Mepivacaine does not ordinarily produce irritation or tissue damage.

Levonordefrin is a sympathomimetic amine used as a vasoconstrictor in local anesthetic solutions. It has pharmacologic activity similar to that of Epinephrine but it is more stable than Epinephrine. In equal concentrations, Levonordefrin is less potent than Epinephrine in raising blood pressure, and as a vasoconstrictor.

INDICATIONS AND USAGE

Mepivacaine is indicated for production of local anesthesia for dental procedures by infiltration or nerve block in adults and pediatric patients.

CONTRAINDICATIONS

Mepivacaine is contraindicated in patients with a known hypersensitivity to amide-type local anesthetics.

WARNINGS

RESUSCITATIVE EQUIPMENT AND DRUGS SHOULD BE IMMEDIATELY AVAILABLE. (See ADVERSE REACTIONS).

Reactions resulting in fatality have occurred on rare occasions with the use of local anesthetics, even in the absence of a history of hypersensitivity.

Fatalities may occur with use of local anesthetics in the head and neck region as the result of retrograde arterial flow to vital CNS areas even when maximum recommended doses are observed. The practitioner should be alert to early evidence of alteration in sensorium or vital signs.

The solution which contains a vasoconstrictor (Mepivacaine HCl 2% (20 mg/mL)) should be used with extreme caution for patients whose medical history and physical evaluation suggest the existence of hypertension, arteriosclerotic heart disease, cerebral vascular insufficiency, heart block, thyrotoxicosis and diabetes, etc.

The solution which contains a vasoconstrictor (Mepivacaine HCl 2% (20 mg/mL)) also contains potassium metabisulfite, a sulfite that may cause allergic-type reactions including anaphylactic symptoms and life-threatening or less severe asthmatic episodes in certain susceptible people. The overall prevalence of sulfite sensitivity in the general population is unknown and probably low. Sulfite sensitivity is seen more frequently in asthmatic than in non-asthmatic people. Mepivacaine HCl 3% (30 mg/mL) is SULFITE FREE.

Mepivacaine, along with other local anesthetics, is capable of producing methemoglobinemia. The clinical signs of methemoglobinemia are cyanosis of the nail beds and lips, fatigue and weakness. If methemoglobinemia does not respond to administration of oxygen, administration of methylene blue intravenously 1-2 mg/kg body weight over a 5 minute period is recommended.

The American Heart Association has made the following recommendations regarding the use of local anesthetics with vasoconstrictors in patients with ischemic heart disease: "Vasoconstrictor agents should be used in local anesthesia solutions during dental practice only when it is clear that the procedure will be shortened or the analgesia rendered more profound. When a vasoconstrictor is indicated, extreme care should be taken to avoid intravascular injection. The minimum possible amount of vasoconstrictor should be used." (Kaplan, EL, editor: Cardiovascular disease in dental practice, Dallas 1986, American Heart Association.)

Methemoglobinemia: Cases of methemoglobinemia have been reported in association with local anesthetic use; MEPIVACAINE, along with other local anesthetics, is capable of producing this condition. Although all patients are at risk for methemoglobinemia, patients with glucose-6-phosphate dehydrogenase deficiency, congenital or idiopathic methemoglobinemia, cardiac or pulmonary compromise, infants under 6 months of age, and concurrent exposure to oxidizing agents or their metabolites are more susceptible to developing clinical manifestations of the condition. If local anesthetics must be used in these patients, close monitoring for symptoms and signs of methemoglobinemia is recommended.

Signs of methemoglobinemia may occur immediately or may be delayed some hours after exposure, and are characterized by cyanosis of the skin, nail beds and lips, and/or abnormal coloration of the blood, fatigue and weakness. Methemoglobin levels may continue to rise; therefore, immediate treatment is required to avert more serious central nervous system and cardiovascular adverse effects, including seizures, coma, arrhythmias, and death. Discontinue MEPIVACAINE and any other oxidizing agents. Depending on the severity of the signs and symptoms, patients may respond to supportive care, i.e., oxygen therapy, hydration. If methemoglobinemia does not respond to administration of oxygen, a more severe clinical presentation may require treatment with methylene blue exchange transfusion, or hyperbaric oxygen.

PRECAUTIONS

The safety and effectiveness of Mepivacaine depend upon proper dosage, correct technique, adequate precautions, and readiness for emergencies.

The lowest dose that results in effective anesthesia should be used to avoid high plasma levels and possible adverse effects. Injection of repeated doses of Mepivacaine may cause significant increases in blood levels with each repeated dose due to slow accumulation of the drug or its metabolites, or due to slower metabolic degradation than normal.

Tolerance varies with the status of the patient. Debilitated, elderly patients, acutely ill patients, and children should be given reduced doses commensurate with their weight and physical status.

Mepivacaine should be used with caution in patients with a history of severe disturbances of cardiac rhythm or heart block.

INJECTIONS SHOULD ALWAYS BE MADE SLOWLY WITH ASPIRATION TO AVOID INTRAVASCULAR INJECTION AND THEREFORE SYSTEMIC REACTION TO BOTH LOCAL ANESTHETIC AND VASOCONSTRICTOR.

If sedatives are employed to reduce patient apprehension, use reduced doses, since local anesthetic agents, like sedatives, are central nervous system depressants which in combination may have an additive effect. Young children should be given minimal doses of each agent.

Changes in sensorium such as excitation, disorientation or drowsiness may be early indications of a high blood level of the drug and may occur following inadvertent intravascular administration or rapid absorption of Mepivacaine.

Local anesthetic procedures should be used with caution when there is inflammation and/or sepsis in the region of the proposed injection.

Information for Patients/Patient Counseling Information:

The patient should be cautioned against loss of sensation and possibility of biting trauma should the patient attempt to eat or chew gum prior to return of sensation. Inform patients that use of local anesthetics may cause methemoglobinemia, a serious condition that must be treated promptly. Advise patients or caregivers to seek immediate medical attention if they or someone in their care experience the following signs or symptoms: pale, gray, or blue colored skin (cyanosis); headache; rapid heart rate; shortness of breath; lightheadedness; or fatigue.

Clinically Significant Drug Interactions

The administration of local anesthetic solutions containing vasopressors, such as Levonordefrin, Epinephrine or Norepinephrine, to patients receiving tricyclic antidepressants or monoamine oxidase inhibitors may produce severe, prolonged hypertension. Concurrent use of these agents should generally be avoided. In situations when concurrent therapy is necessary, careful patient monitoring is essential. Concurrent administration of vasopressor drugs and of ergot-type oxytocic drugs may cause severe, persistent hypertension or cerebrovascular accidents.

Phenothiazines and butyrophenones may reduce or reverse the pressor effect of Epinephrine.

Solutions containing a vasoconstrictor should be used cautiously in the presence of disease which may adversely affect the patient's cardiovascular system. Serious cardiac arrhythmias may occur if preparations containing a vasoconstrictor are employed in patients during or following the administration of potent inhalation anesthetics.

Patients who are administered local anesthetics are at increased risk of developing methemoglobinemia when concurrently exposed to the following drugs, which could include other local anesthetics:

EXAMPLES OF DRUGS ASSOCIATED WITH METHEMOGLOBINEMIA:
Class | Examples
Nitrates/Nitrites | nitric oxide, nitroglycerin, nitroprus-side, nitrous oxide
Local anesthetics | articaine, benzocaine, bupivacaine, lidocaine, mepivacaine, prilocaine, procaine, ropivacaine, tetracaine
Antineoplastic Agents | cyclophosphamide, flutamide, hy-droxyurea, ifosfamide, rasburicase
Antibiotics | dapsone, nitrofurantoin, para-aminosalicylic acid, sulfonamides
Antimalarials | chloroquine, primaquine
Anticonvulsants | Phenobarbital, phenytoin, sodium valproate
Other drugs | acetaminophen, metoclopramide, quinine, sulfasalazine

MEPIVACAINE SHOULD BE USED WITH CAUTION IN PATIENTS WITH KNOWN DRUG ALLERGIES AND SENSITIVITIES. A thorough history of the patient's prior experience with Mepivacaine or other local anesthetics as well as concomitant or recent drug use should be taken (see CONTRAINDICATIONS). Patients allergic to methylparaben or para-aminobenzoic acid derivatives (procaine, tetracaine, benzocaine, etc.) have not shown cross-sensitivity to agents of the amide type such as Mepivacaine. Since Mepivacaine is metabolized in the liver and excreted by the kidneys, it should be used cautiously in patients with liver and renal disease.

Carcinogenesis, Mutagenesis, Impairment of Fertility

Studies of Mepivacaine HCl in animals to evaluate the carcinogenic and mutagenic potential or the effect on fertility have not been conducted.

Pregnancy

Teratogenic Effects

Pregnancy Category C

Animal reproduction studies have not been conducted with this solution. It is also not known whether this solution can cause fetal harm when administered to a pregnant woman or can effect reproductive capacity. This solution should be given to a pregnant woman only if clearly needed.

Nursing Mothers

It is not known whether this drug is excreted in human milk. Because many drugs are excreted in human milk, caution should be exercised when this solution is administered to a nursing woman.

Pediatric Use

Great care must be exercised in adhering to safe concentrations and dosages for pedodontic administration (see DOSAGE AND ADMINISTRATION).

ADVERSE REACTIONS

Reactions to MEPIVACAINE are characteristic of those associated with other amide-type local anesthetics. Systemic adverse reactions involving the central nervous system and the cardiovascular system usually result from high plasma levels (which may be due to excessive dosage, rapid absorption, inadvertent intravascular injection, or slow metabolic degradation), injection technique, or volume of injection.

A small number of reactions may result from hypersensitivity, idiosyncrasy or diminished tolerance to normal dosage on the part of the patient.

Persistent paresthesias of the lips, tongue, and oral tissues have been reported with the use of mepivacaine, with slow, incomplete, or no recovery. These post-marketing events have been reported chiefly following nerve blocks in the mandible and have involved the trigeminal nerve and its branches.

Reactions involving the central nervous system are characterized by excitation and/or depression. Nervousness, dizziness, blurred vision, or tremors may occur followed by drowsiness, convulsions, unconsciousness, and possible respiratory arrest. Since excitement may be transient or absent, the first manifestations may be drowsiness merging into unconsciousness and respiratory arrest.

Cardiovascular reactions are depressant. They may be the result of direct drug effect or more commonly in dental practice, the result of vasovagal reaction, particularly if the patient is in the sitting position. Failure to recognize premonitory signs such as sweating, feeling of faintness, changes in pulse or sensorium may result in progressive cerebral hypoxia and seizure or serious cardiovascular catastrophe. Management consists of placing the patient in the recumbent position and administration of oxygen. Vasoactive drugs such as Ephedrine or Methoxamine may be administered intravenously.

Allergic reactions are rare and may occur as a result of sensitivity to the local anesthetic and are characterized by cutaneous lesions of delayed onset or urticaria, edema and other manifestations of allergy. The detection of sensitivity by skin testing is of limited value. As with other local anesthetics, anaphylactoid reactions to Mepivacaine have occurred rarely. The reaction may be abrupt and severe and is not usually dose related. Localized puffiness and swelling may occur.

OVERDOSAGE

Treatment of a patient with toxic manifestations consists of assuring and maintaining a patent airway and supporting ventilation (respiration) as required. This usually will be sufficient in the management of most reactions. Should a convulsion persist despite ventilatory therapy, small increments of anticonvulsive agents may be given intravenously, such as benzodiazephine (e.g., diazepam) or ultrashort-acting barbiturates (e.g., thiopental or thiamylal) or short-acting barbiturates (e.g., pentobarbital or secobarbital). Cardiovascular depression may require circulatory assistance with intravenous fluids and/or vasopressor (e.g., Ephedrine) as dictated by the clinical situation. Allergic reactions should be managed by conventional means.

IV and SC LD50's in mice for Mepivacaine Hydrochloride 3% are 33 and 258 mg/kg, respectively. The acute IV and SC LD50's in mice for Mepivacaine Hydrochloride 2% with Levonordefrin 1:20,000 are 30 and 184 mg/kg, respectively.

DOSAGE AND ADMINISTRATION

As with all local anesthetics, the dose varies and depends upon the area to be anesthetized, the vascularity of the tissues, individual tolerance and the technique of anesthesia. The lowest dose needed to provide effective anesthesia should be administered. For specific techniques and procedures refer to standard dental manuals and textbooks.

For infiltration and block injections in the upper or lower jaw, the average dose of 1 cartridge will usually suffice.

Each cartridge contains 1.7 mL (34 mg of 2% or 51 mg of 3%).

5.3 cartridges (180 mg of the 2% solution or 270 mg of the 3% solution) are usually adequate to effect anesthesia of the entire oral cavity. Whenever a larger dose seems to be necessary for an extensive procedure, the maximum dose should be calculated according to the patient's weight. A dose of up to 3 mg per pound of body weight may be administered. At any single dental sitting the total dose for all injected sites should not exceed 400 mg in adults.

The maximum pediatric dose should be carefully calculated.

Maximum dose for pediatric population =

Child's Weight (lbs.) | × | Maximum Recommended Dose
150 | × | for Adults (400 mg)

The following table, approximating these calculations, may also be used as a guide. This table is based upon a recommended maximum for larger pediatric population of 5.3 cartridges (the maximum recommended adult dose) during any single dental sitting, regardless of the pediatric patient's weight or (for 2% mepivacaine) calulated maximum amount of drug:

Maximum Allowable Dosage [Adapted from Malamed, Stanley F: Handbook of medical emergencies in the dental office, ed. 2, St. Louis, 1982. The C.V. Mosby Co.]
 | 3% Mepivacaine |  | 2% Mepivacaine 1:20,000 Levonordefrin
 | 3 mg/lb (270 mg max.) |  | 3mg/lb (180 mg max.)
Weight (lb.) | mg | Number of Cartridges | mg | Number of Cartridges
20 | 60 | 1.2 | 60 | 1.8
30 | 90 | 1.8 | 90 | 2.6
40 | 120 | 2.3 | 120 | 3.5
50 | 150 | 2.9 | 150 | 4.4
60 | 180 | 3.5 | 180 | 5.3
80 | 240 | 4.7 | 180 | 5.3
100 | 270 | 5.3 | 180 | 5.3
120 | 270 | 5.3 | 180 | 5.3

When using Mepivacaine HCl injection USP for infiltration or regional block anesthesia, injection should always be made slowly and with frequent aspiration.

Any unused portion of a cartridge should be discarded.

Parenteral drug products should be inspected visually for particulate matter and discoloration prior to administration, whenever solution and container permit.

DISINFECTION OF CARTRIDGES

As in the case of any cartridge, the diaphragm should be disinfected before needle puncture. The diaphragm should be thoroughly swabbed with either pure 91% isopropyl alcohol or 70% ethyl alcohol, USP, just prior to use. Many commercially available alcohol solutions contain ingredients which are injurious to container components, and therefore, should not be used. Cartridges should not be immersed in any solution.

HOW SUPPLIED

Mepivacaine HCl 3% (30 mg/mL); (Mepivacaine Hydrocholoride Injection USP) is available in cardboard boxes containing 5 blisters of 10 × 1.7 mL single-dose dental cartridges, 50 per carton. Mepivacaine HCl 2% (20 mg/mL) (Mepivacaine Hydrochloride and Levonordefrin Injection; USP) is available in cardboard boxes containing 5 blisters of 10 × 1.7 mL single-dose dental cartridges, 50 per carton.

STORAGE AND HANDLING

Both solutions should be stored at controlled room temperature, below 25° C (77° F). Protect from light. Do not permit to freeze. BOXES: For protection from light, retain in box until time of use. Once opened, the box should be reclosed by closing the top flap. The Mepivacaine 2% (20 mg/mL) solution should not be used if its color is pinkish or darker than slightly yellow or it contains a precipitate. Cartridge warmers should not be used with Mepivacaine HCl injection USP products.

Manufactured and Distributed by
Novocol Pharmaceutical of Canada, Inc.
Cambridge, Ontario, N1R 6X3, Canada

Rev. 03/2020 (2780-3)

PRINCIPAL DISPLAY PANEL - 3% Cartridge Carton

HENRY SCHEIN®

NDC 0404-6730-05

MEPIVACAINE HCl 3% (30 mg/mL)
INJECTION

without VASOCONSTRICTOR

(MEPIVACAINE HCl INJECTION, USP)

50 Single-Dose Cartridges • 1.7 mL Minimum

Rx Only